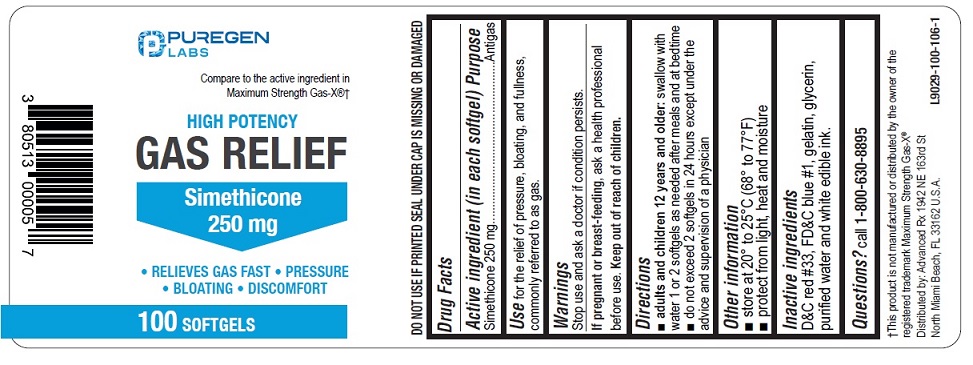 DRUG LABEL: Gas Relief
NDC: 80513-112 | Form: CAPSULE, LIQUID FILLED
Manufacturer: Advanced Rx LLC
Category: otc | Type: HUMAN OTC DRUG LABEL
Date: 20240830

ACTIVE INGREDIENTS: DIMETHICONE 250 mg/1 1
INACTIVE INGREDIENTS: D&C RED NO. 33; FD&C BLUE NO. 1; GELATIN; GLYCERIN; WATER

Active ingredient (in each softgel)

Simethicone 250 mg

Purpose

Antigas

Use

for the relief of pressure, bloating, and fullness, commonly referred to as gas.

Stop use and ask a doctor if condition persists

KEEP OUT OF REACH OF CHILDREN

If pregnant or breast-feeding,ask a health professional before use.

Keep out of reach of children.

Directions

- adults and children 12 years and older:swallow with water 1 or 2 softgels as needed after meals and at bedtime
- do not exceed 2 softgels in 24 hours except under the advice and supervision of a physician

Other information

- store at 20° to 25°C (68° to 77°F)
- protect from light, heat and moisture
- DO NOT USE IF PRINTED SEAL UNDER CAP IS MISSING OR DAMAGED

Inactive ingredients

D&C red #33, FD&C blue #1, gelatin, glycerin, purified water and white edible ink.

Questions?

call 1-800-630-8895

Distributed by:

Advanced Rx LLC

1942 NE 163rd St North Miami Beach,

FL 33162 U.S.A.

PACKAGE LABEL

NDC 80513-112-01

Compare to the active ingredient in Maximum Strength Gas-X®†

HIGH POTENCY

GAS RELIEF

Simethicone 250 mg

• RELIEVES GAS FAST

• PRESSURE

• BLOATING

• DISCOMFORT

100 SOFTGELS

†This product is not manufactured or distributed by the owner of the registered trademark Maximum Strength Gas-X®